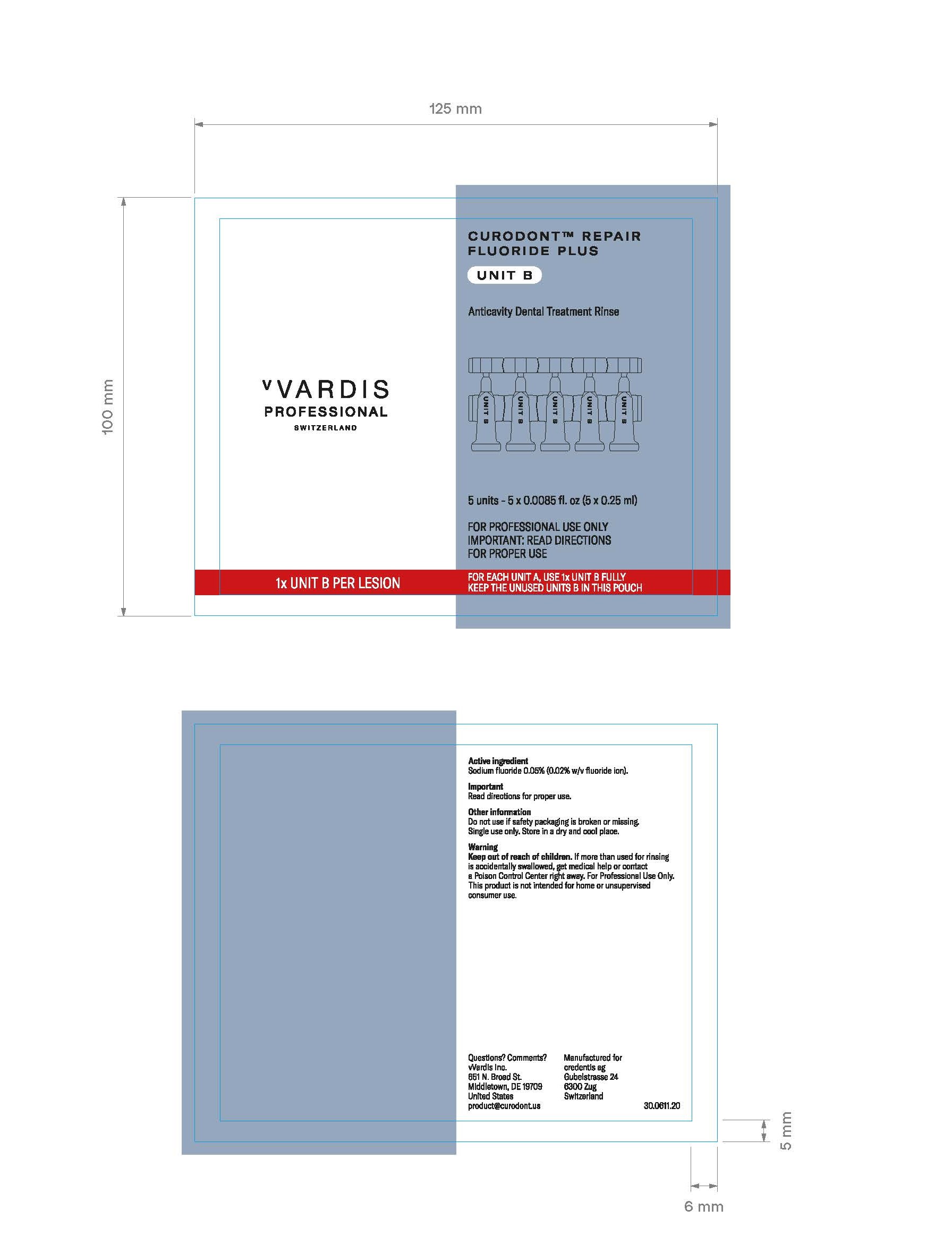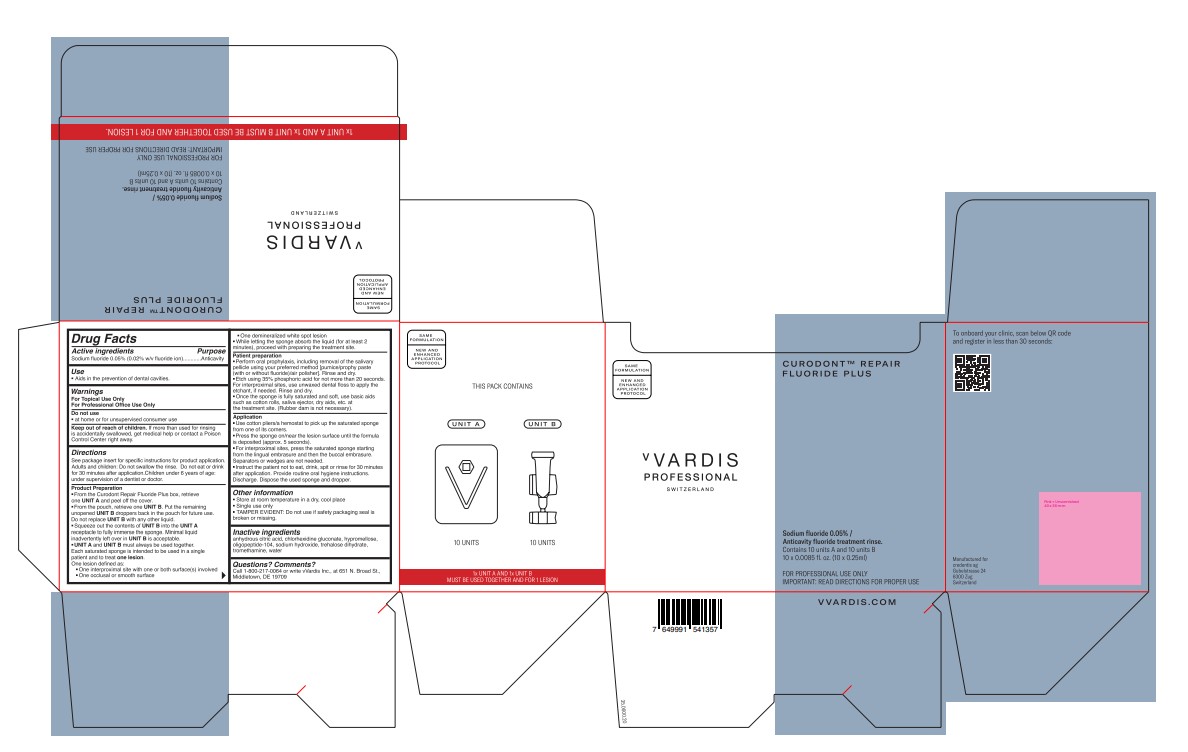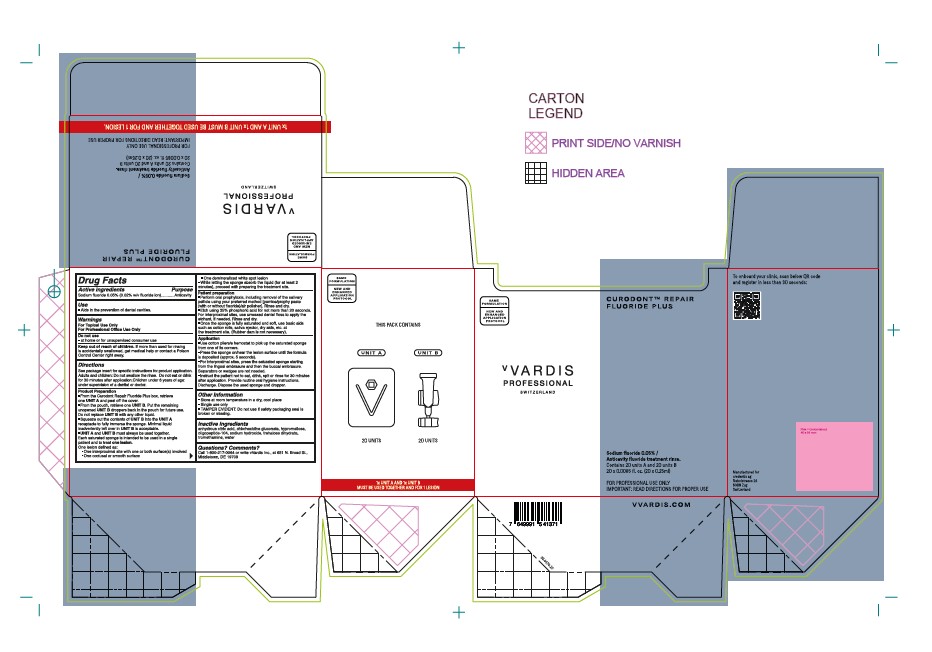 DRUG LABEL: CURODONT REPAIR FLUORIDE PLUS
NDC: 72247-108 | Form: SPONGE
Manufacturer: CREDENTIS AG
Category: otc | Type: HUMAN OTC DRUG LABEL
Date: 20250623

ACTIVE INGREDIENTS: SODIUM FLUORIDE 0.02 g/100 mL
INACTIVE INGREDIENTS: OLIGOPEPTIDE-104; TROMETHAMINE; HYPROMELLOSES; SODIUM HYDROXIDE; CHLORHEXIDINE GLUCONATE; WATER; ANHYDROUS CITRIC ACID; TREHALOSE DIHYDRATE

CREDENTIS (Gen 3) - vVardis Professional - CURODONT REPAIR FLUORIDE PLUS (72247-108)

ACTIVE INGREDIENTS

SODIUM FLUORIDE 0.05% (0.02% W/V FLUORIDE ION)

PURPOSE

ANTICAVITY

USES

AIDS IN THE PREVENTION OF DENTAL CAVITIES.

- ANTICAVITY DENTAL RINSE
- ENAMEL MINERALIZER
- REPAIRS WHITE SPOTS

WARNINGS

WARNINGS

FOR TOPICAL USE ONLY.

WARNINGS

FOR PROFESSION OFFICE USE ONLY

DO NOT USE

- AT HOME OR FOR UNSUPERVISED CONSUMER USE

KEEP OUT OF REACH OF CHILDREN. IF MORE THAN USED FOR RINSING IS ACCIDENTALLY SWALLOWED, GET MEDICAL HELP OR CONTACT A POISON CONTROL CENTER RIGHT AWAY.

DIRECTIONS

- See package insert for specific instructions for product activation
- From the Curodont Repair Fluoride Plus box, retrieve one UNIT A and peel off the color.
- From the pouch, retrieve one UNIT B. Keep the remaining unused UNIT B in the pouch for future use. Do not replace UNIT B with water, saline, or any other liquid. UNIT A and UNIT B are intended to always be used together.
- Pour the entire contents of UNIT B into the UNIT A receptacle containing the sponge, letting it absorb the liquid for at least 5 minutes to fully activate the proprietary formulation. Meanwhile, proceed with preparing the treatment site. Each set of UNIT A and UNIT B is intended to treat one initial lesion in a single patient.
- Perform oral prophylaxis on the teeth to be treated, including removal of the salivary pellicle using your preferred method (pumice/prophy paste/air polisher/2% sodium hypochlorite). Rinse and dry.
- Etch using 35% phosphoric acid for 20 seconds. For interproximal sites, use unwaxed dental floss to apply the etchant, if needed. Rinse.
- After ensuring that the sponge in UNIT A is fully soaked and soft, isolate the treatment site using basic aids such as cotton rolls, saliva ejector, dry aids, etc. Rubber dam is not necessary.
- Use cotton pliers to firmly grip the saturated sponge in UNIT A from one of its corners.
- Press the sponge on the lesion surface until the formula is deposited and hte sponge starts to appear dry. Use only saturated sponge per lesion. One 'lesion' is defined as one lesion on occlusal/buccal/lingual surfaces or one interproximal site with lesions on one or both adjacent surfaces.
- For interproximal sites, press the saturated sponge starting from lingual embrasure, moving to the buccal and, for any residual formula, the occlusal. Separators or wedges are not needed.
- Wait for 5 minutes before asking the patient to expectorate residues, if any. Dispose the used UNIT A and UNIT B.
- Instruct the patient not to rinse, eat or drink for 30 minutes.

Other information

- Store at room temperature in a dry, cool place
- Single use only
- TAMPER EVIDENT: Do not use if safety packaging seal is broken or missing.

Inactive Ingredients

anhydrous citric acid, chlorhexidine gluconate, hypromellose, oligopeptide-104, sodium hydroxide, trehalose dihydrate, tromethamine, water

Questions? Comments?

Call 1-800-217-0064 or write vVardis Inc., at 651 N. Broad St., Middletown, DE 19709

DOSAGE AND ADMINISTRATION

Anticavity dental treatment rinse. Contains 10 units A and 10 units B

10 x 0.0085 fl. oz. (10 x 0.25 ml)